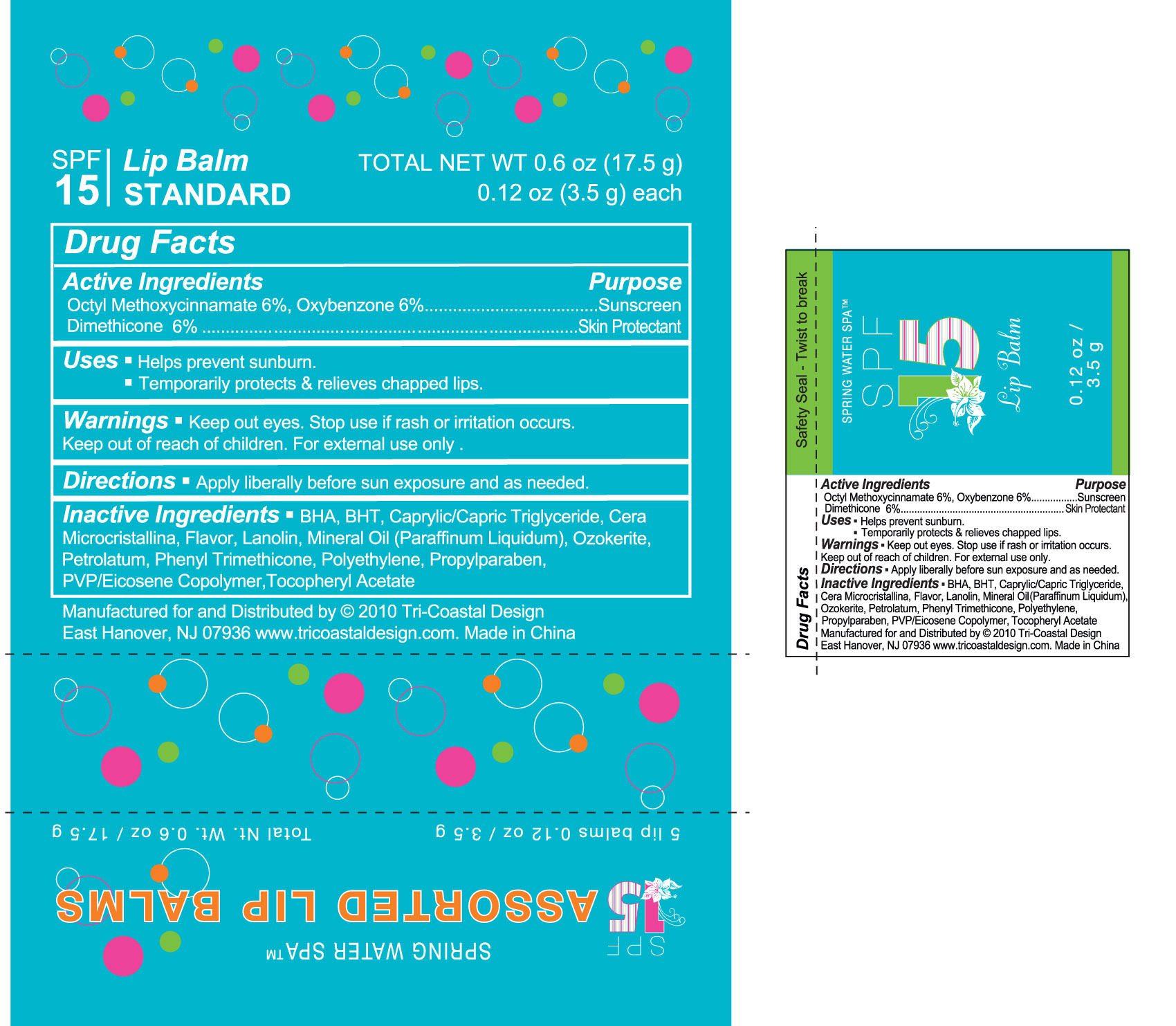 DRUG LABEL: Lip Balm
NDC: 49852-202 | Form: LIPSTICK
Manufacturer: Tri-Coastal Design Company Inc. 
Category: otc | Type: HUMAN OTC DRUG LABEL
Date: 20100212

ACTIVE INGREDIENTS: OCTINOXATE 6 g/100 g; OXYBENZONE 6 g/100 g; DIMETHICONE 6 g/100 g
INACTIVE INGREDIENTS: BUTYLATED HYDROXYANISOLE; BUTYLATED HYDROXYTOLUENE; MEDIUM-CHAIN TRIGLYCERIDES; LANOLIN; MINERAL OIL; PETROLATUM; PHENYL TRIMETHICONE; PROPYLPARABEN

Drug Facts

Active Ingredient

Octyl Methoxycinnamate 6%

Oxybenzone 6%

Dimethicone 1%

Purpose

Sunscreen
Skin Protectant

Uses

- Helps prevent sunburn
- Temporarily protects and relieves chapped lips

Warnings

- Keep out of eyes. Stop use if rash or irritation occurs. Keep out of reach of children. For external use only.

Directions

- Apply liberally before sun exposure and as needed.

Inactive Ingredients

BHA, BHT, Caprylic/Capric Triglyceride, Cera Microcristallina, Flavor, Lanolin, Mineral Oil (Paraffinum Liquidum), Ozokerite, Petrolatum, Phenyl Trimethicone, Polyethylene, Propylparaben, PVP/Eicosene Copolymer, Tocopheryl Acetate

Package Label